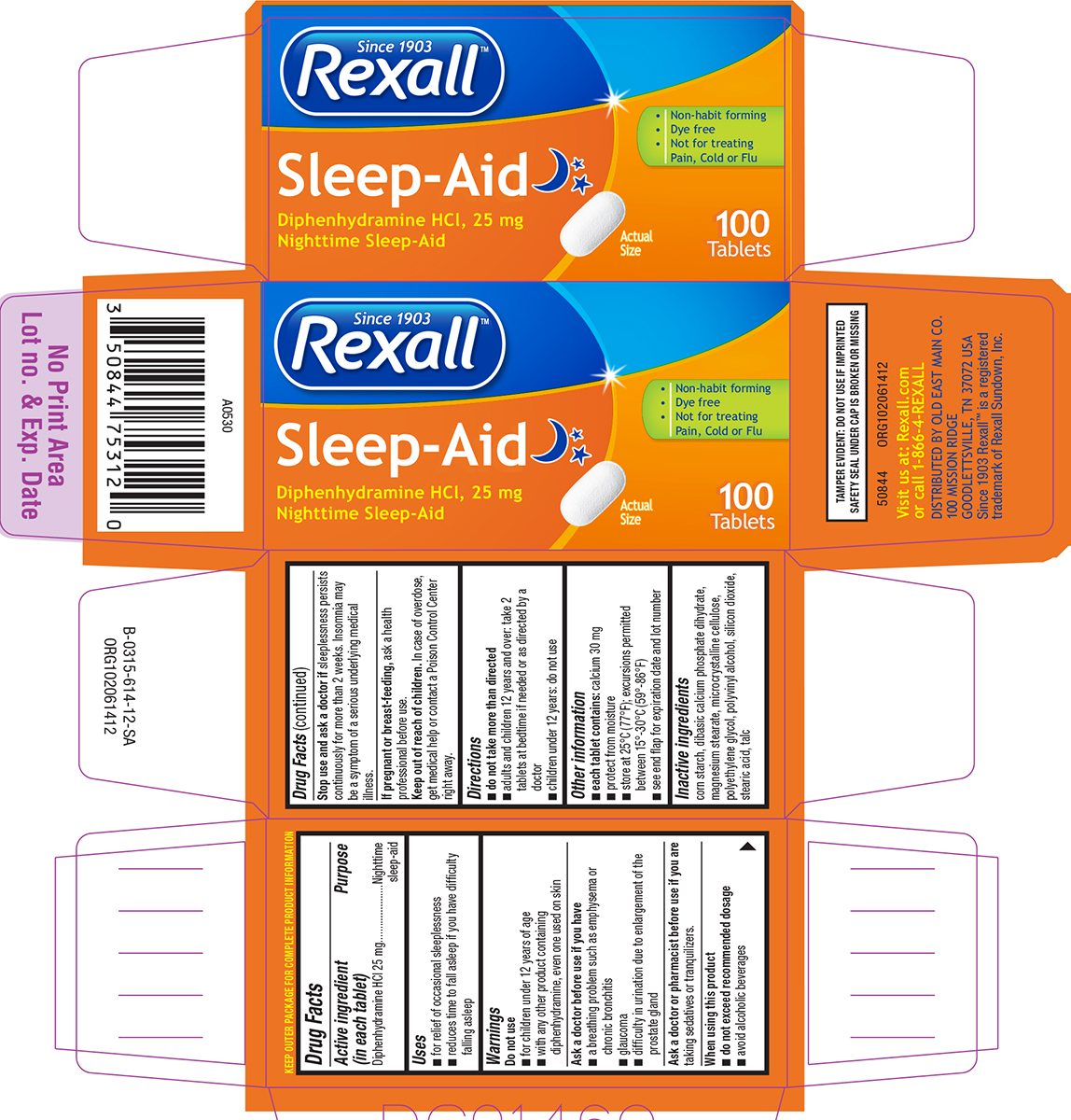 DRUG LABEL: Sleep Aid
NDC: 55910-614 | Form: TABLET, FILM COATED
Manufacturer: DOLGENCORP, LLC
Category: otc | Type: HUMAN OTC DRUG LABEL
Date: 20250815

ACTIVE INGREDIENTS: DIPHENHYDRAMINE HYDROCHLORIDE 25 mg/1 1
INACTIVE INGREDIENTS: STARCH, CORN; DIBASIC CALCIUM PHOSPHATE DIHYDRATE; MAGNESIUM STEARATE; MICROCRYSTALLINE CELLULOSE; POLYETHYLENE GLYCOL, UNSPECIFIED; POLYVINYL ALCOHOL, UNSPECIFIED; SILICON DIOXIDE; STEARIC ACID; TALC

Rexall 44-614-SA

Active ingredient (in each tablet)

Diphenhydramine HCl 25 mg

Purpose

Nighttime sleep-aid

Uses

- for relief of occasional sleeplessness
- reduces time to fall asleep if you have difficulty falling asleep

Warnings

Do not use

- for children under 12 years of age
- with any other product containing diphenhydramine, even one used on skin

Ask a doctor before use if you have

- a breathing problem such as emphysema or chronic bronchitis
- difficulty in urination due to enlargement of the prostate gland
- glaucoma

Ask a doctor or pharmacist before use if you are

taking sedatives or tranquilizers.

When using this product

- do not exceed recommended dosage
- avoid alcoholic beverages

Stop use and ask a doctor if

sleeplessness persists continuously for more than 2 weeks. Insomnia may be a symptom of a serious underlying medical illness.

If pregnant or breast-feeding,

ask a health professional before use.

Keep out of reach of children.

In case of overdose, get medical help or contact a Poison Control Center right away.

Directions

- do not take more than directed
- adults and children 12 years and over: take 2 tablets at bedtime if needed or as directed by a doctor
- children under 12 years: do not use

Other information

- each tablet contains: calcium 30 mg
- store at 25°C (77°F); excursions permitted between 15°-30°C (59°-86°F)
- protect from moisture
- see end flap for expiration date and lot number

Inactive ingredients

corn starch, dibasic calcium phosphate dihydrate, magnesium stearate, microcrystalline cellulose, polyethylene glycol, polyvinyl alcohol, silicon dioxide, stearic acid, talc

Principal display panel

Since 1903
Rexall™

Sleep-Aid
Diphenhydramine HCl, 25 mg
Nighttime Sleep-Aid

• Non-habit forming
• Dye free
• Not for treating
Pain, Cold or Flu

Actual
Size

100
Tablets

TAMPER EVIDENT: DO NOT USE IF IMPRINTED
SAFETY SEAL UNDER CAP IS BROKEN OR MISSING

50844 ORG102061412
Visit us at: Rexall.com
or call 1-866-4-REXALL

DISTRIBUTED BY OLD EAST MAIN CO.
100 MISSION RIDGE
GOODLETTSVILLE, TN 37072 USA
Since 1903 Rexall™ is a registered
trademark of Rexall Sundown, Inc.

Rexall 44-614